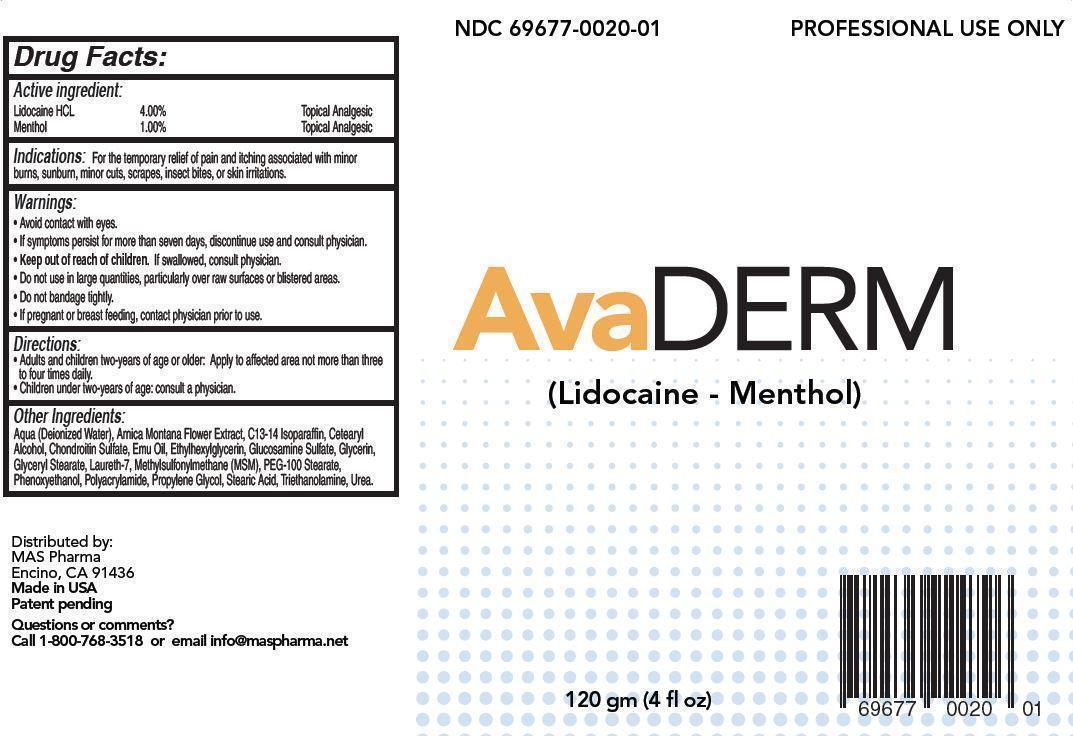 DRUG LABEL: AvaDerm
NDC: 69677-020 | Form: CREAM
Manufacturer: MAS Management Group Inc.
Category: otc | Type: HUMAN OTC DRUG LABEL
Date: 20150702

ACTIVE INGREDIENTS: LIDOCAINE HYDROCHLORIDE 4 g/100 g; MENTHOL 1 g/100 g
INACTIVE INGREDIENTS: WATER; ARNICA MONTANA FLOWER; C13-14 ISOPARAFFIN; CETOSTEARYL ALCOHOL; CHONDROITIN SULFATE (BOVINE); EMU OIL; ETHYLHEXYLGLYCERIN; GLUCOSAMINE SULFATE; GLYCERIN; GLYCERYL STEARATE SE; LAURETH-7; DIMETHYL SULFONE; PEG-100 STEARATE; PHENOXYETHANOL; POLYACRYLAMIDE (10000 MW); PROPYLENE GLYCOL; STEARIC ACID; TROLAMINE; UREA

Active Ingredient:

Lidocaine HCL 4.00% Topical Analgesic

Menthol 1.00% Topical Analgesic

PURPOSE

Indications: For the temporary relief of pain and itching associated with minor burns, sunburn, minor cuts, scrapes, insect bites, or skin irritations.

Keep out of reach of children. If swallowed, consult physician.

INDICATIONS AND USAGE

AvaDerm

(Lidocaine - Menthol)

Directions:

- Adults and children two-years of age or older: Apply to affected area not more than three to four times daily.
- Children under two-years of age: consult a physician.

Warnings:

- Avoid contact with eyes.
- If symptoms persist for more than seven days, discontinue use and consult physician.
- Do not use in large quantities, particularly over raw surfaces or blistered areas.
- Do not bandage tightly.
- If pregnant or breast feeding, contact physician prior to use.

INACTIVE INGREDIENT

Other Ingredients:

aqua (deionized water), arnica montana flower extract, C13-14 isoparaffin, cetearyl alcohol, chondroitin sulfate, emu oil, ethylhexylglycerin, glucosamine sulfate, glycerin, glyceryl stearate, laureth-7, methylsulfonylmethane (MSM), PEG-100 stearate, phenoxyethanol, polyacrylamide, propylene glycol, stearic acid, triethanolamine, urea.